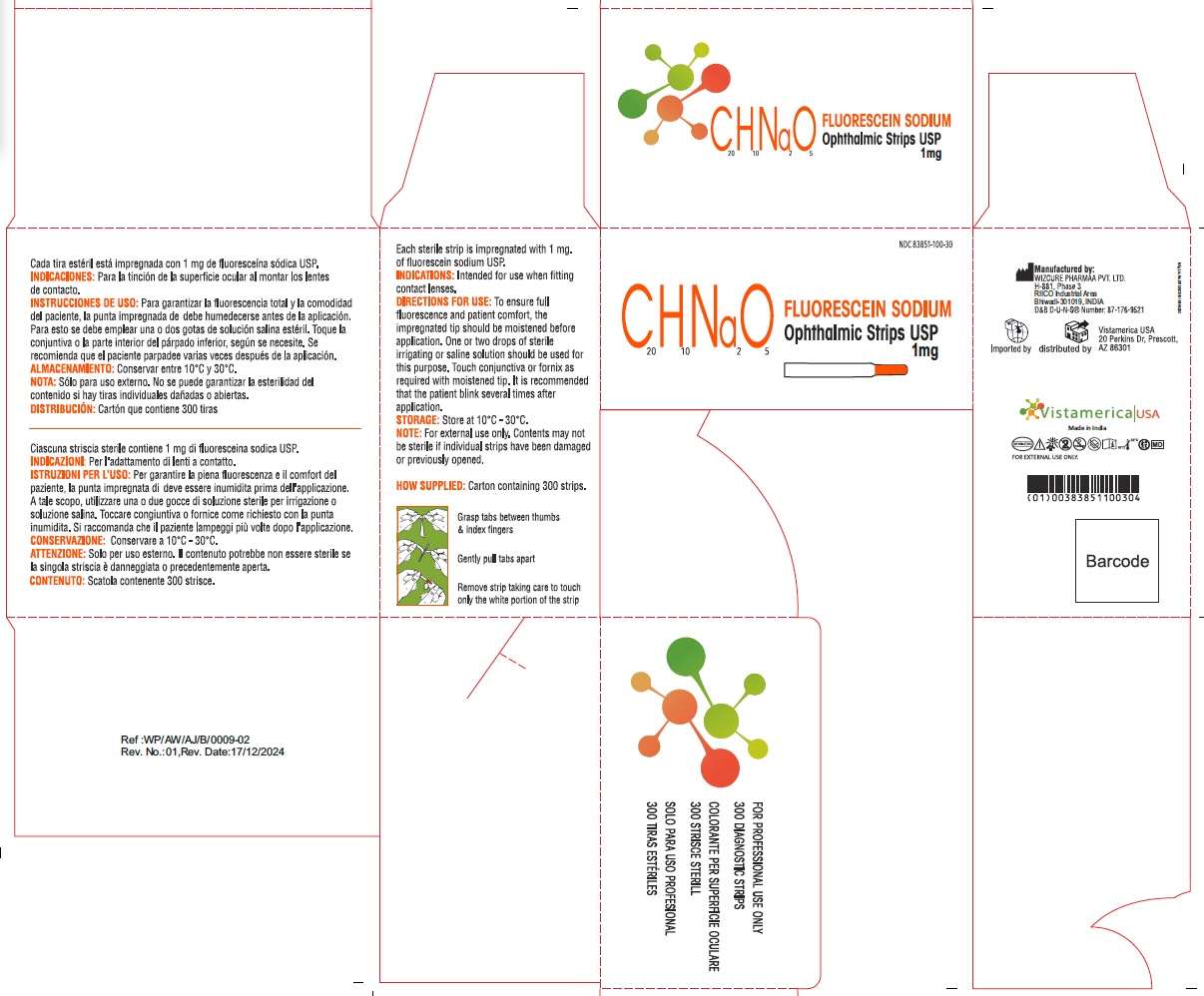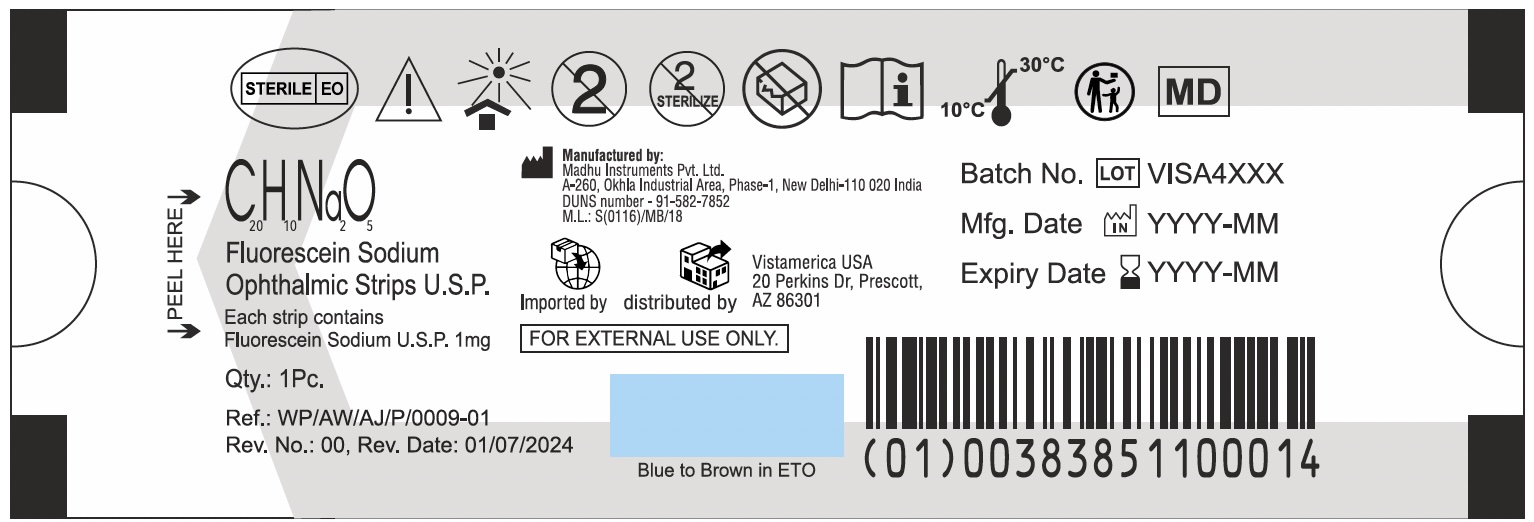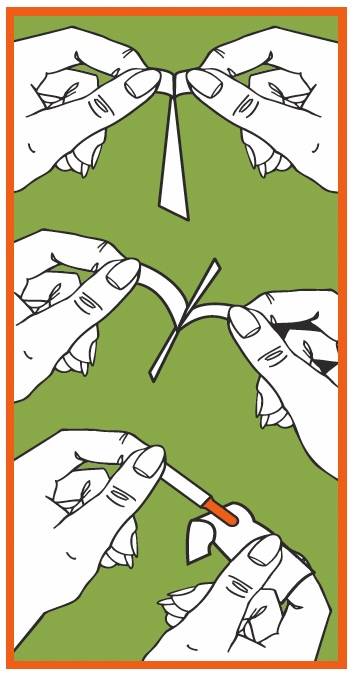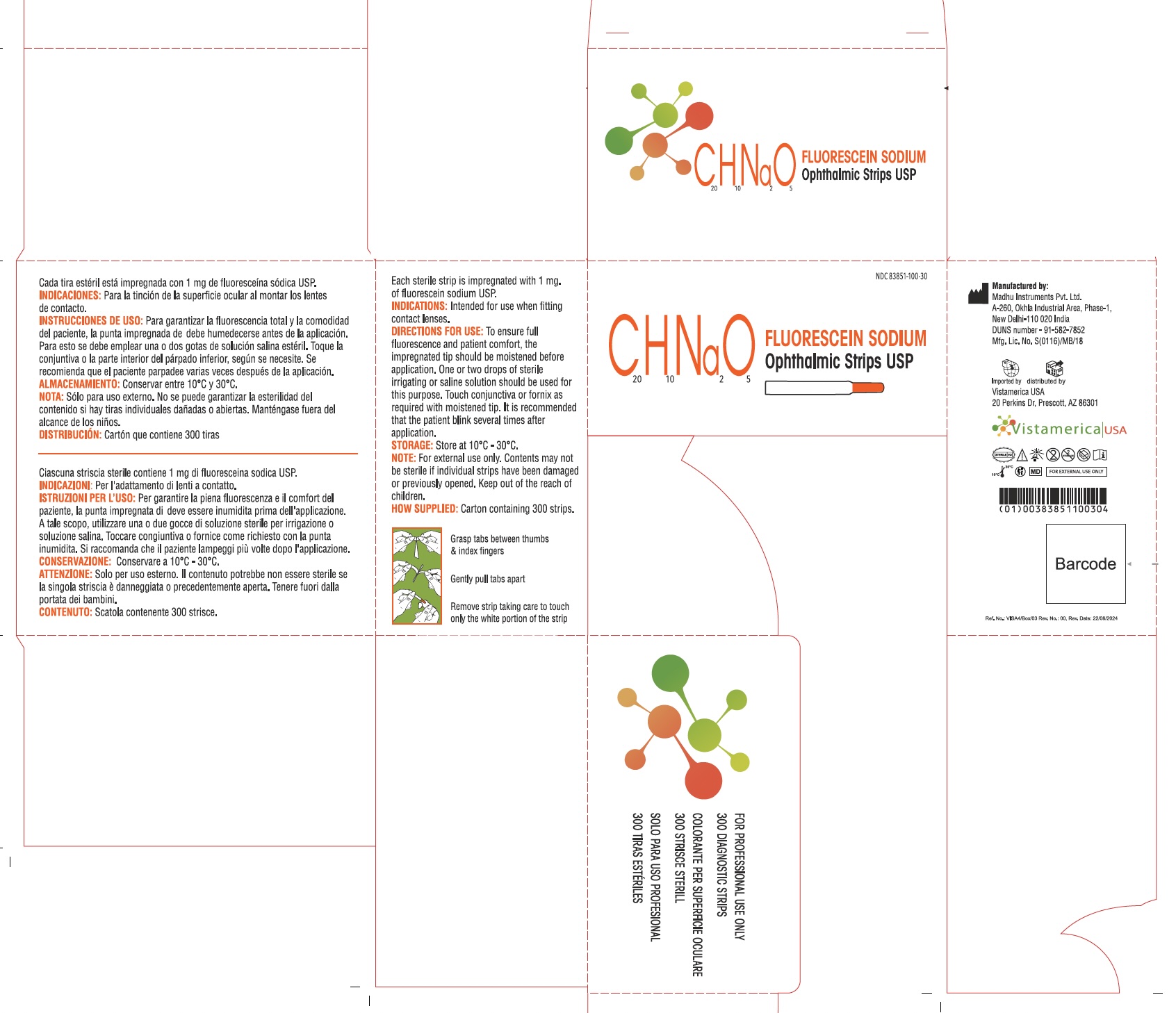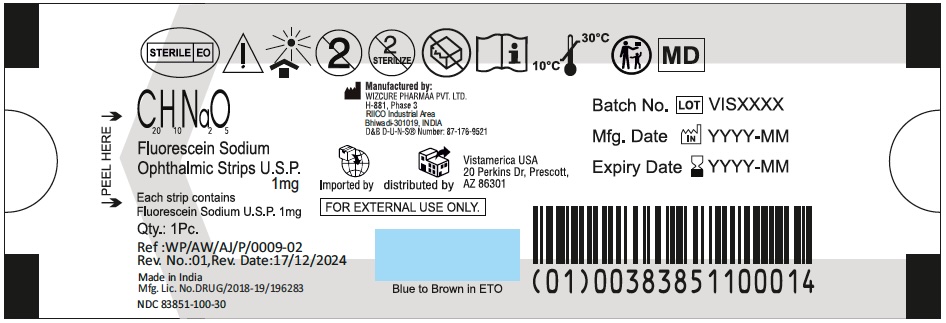 DRUG LABEL: C20H10Na2O5 Fluorescein Sodium Ophthalmic Strips
NDC: 83851-100 | Form: STRIP
Manufacturer: Vistamerica USA
Category: prescription | Type: HUMAN PRESCRIPTION DRUG LABEL
Date: 20250601

ACTIVE INGREDIENTS: FLUORESCEIN SODIUM 1 mg/1 mg

Fluorescein Sodium Ophthalmic Strips

Product Facts

Each sterile strip is impregnated with 1 mg. of fluorescein sodium U.S.P.

INDICATIONS:

Intended for use when fitting contact lenses.

DIRECTIONS FOR USE:

To insure full fluorescence and patient comfort, the impregnated tip should be moistened before application. One or two drops of sterile irrigating or saline solution should be used for this purpose. Touch conjunctiva or fornix as required with moistened tip. It is recommended that the patient blink several times after application.

Grasp tabs between thumbs & index fingers

Gently pull tabs apart

Remove strip taking care to touch only the white portion of the strip

STORAGE:

Store at 10oC - 30oC.

NOTE:

For external use only. Contents may not be sterile if individual strips have been damaged or previously opened.

Keep out of reach of children

HOW SUPPLIED:

Dispenser carton containing 50, 100, or 300 strips.

Manufactured by:

Madhu Instruments Pvt. Ltd.

A-260, Okhla Industrial Area, Phase-1, New Delhi-110 020 India

DUNS number - 91-582-7852

M.L.: S(0116)/MB/18

and

Wizcure Pharmaa Pvt. Ltd.

H-881, Phase 3

RIICO Industrial Area

Bhiwadi-301019, India

DUNS Number: 87-176-9521

Imported and distributed by:

Vistamerica USA

20 Perkins Dr, Prescott

AZ 86301

Representative Packaging:

83851-100: Fluorescein Sodium Ophthalmic Strip Individual Pouch (Wizcure) (above)

83851-100: Fluorescein Sodium Ophthalmic Strip Box (Wizcure) (above)

83851-100: Fluorescein Sodium How Used (above) 83851-100: Fluorescein Sodium Ophthalmic Strip Box (above)

83851-100: Fluorescein Sodium Ophthalmic Strip Individual Pouch (above)